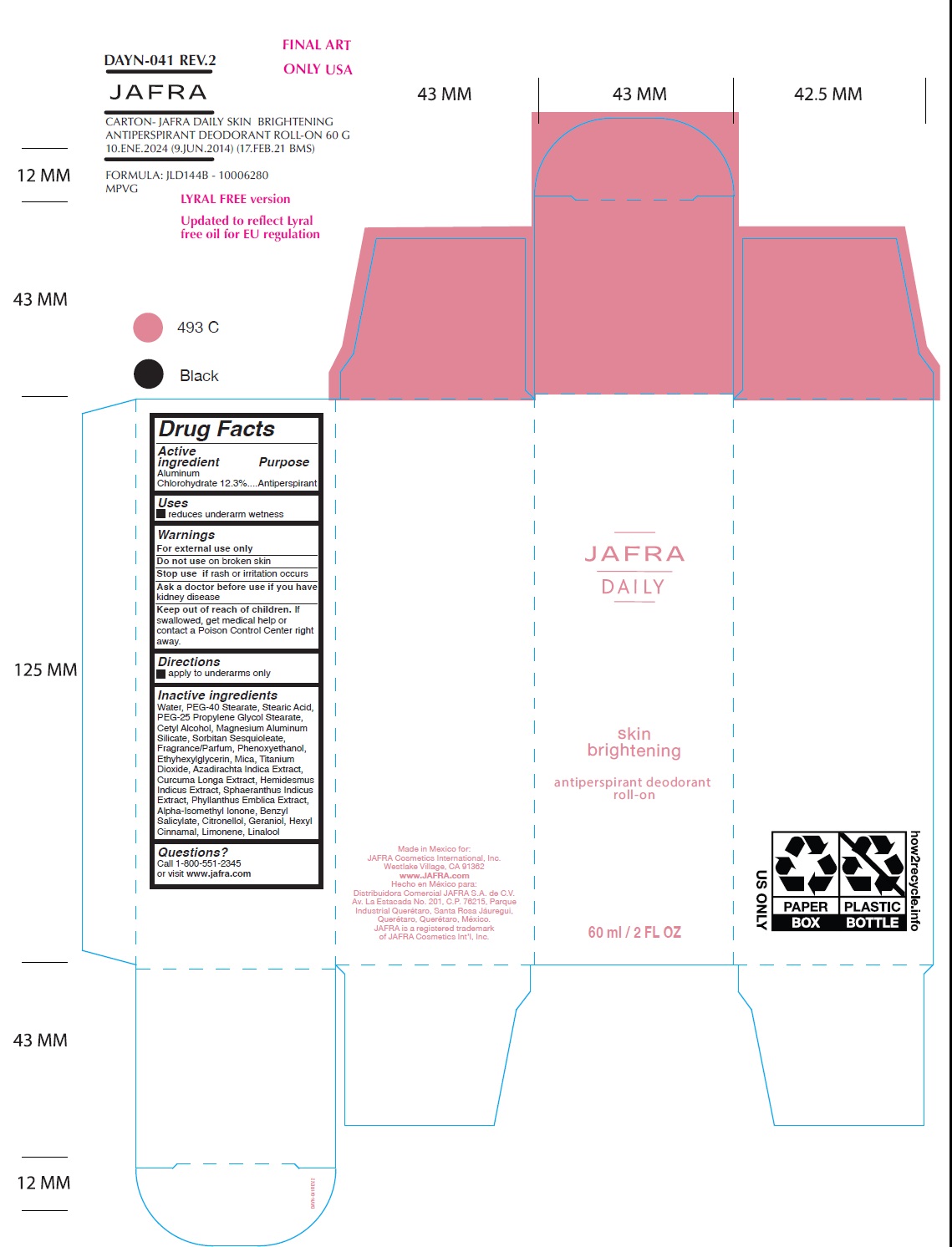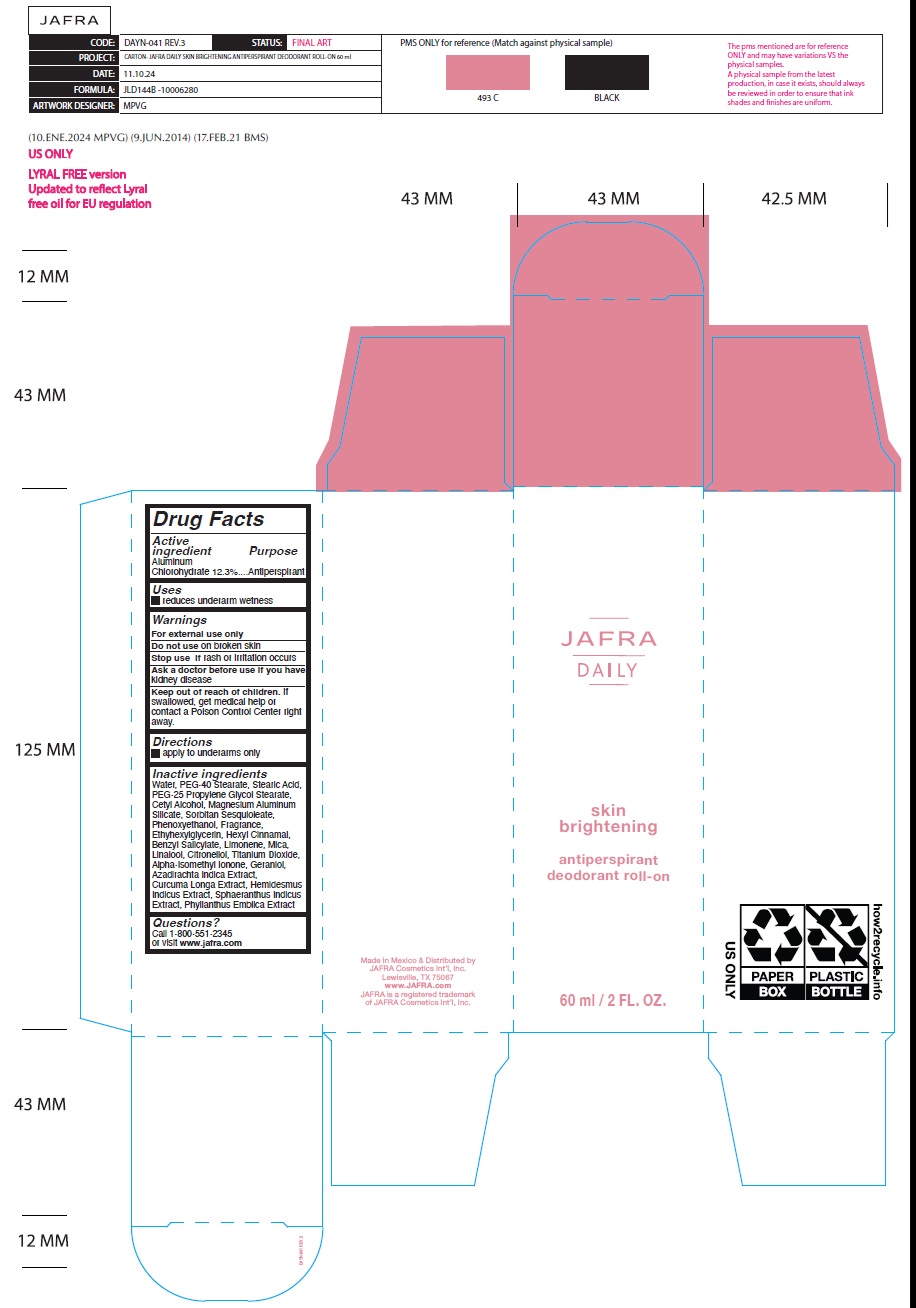 DRUG LABEL: Jafra Daily Skin Brightening Antiperspirant Deodorant Roll-on
NDC: 68828-759 | Form: LIQUID
Manufacturer: Distribuidora Comercial Jafra, S.A. de C.V.
Category: otc | Type: HUMAN OTC DRUG LABEL
Date: 20250109

ACTIVE INGREDIENTS: ALUMINUM CHLOROHYDRATE 12.3 g/100 mL
INACTIVE INGREDIENTS: WATER; PEG-40 STEARATE; STEARIC ACID; PEG-25 PROPYLENE GLYCOL STEARATE; CETYL ALCOHOL; MAGNESIUM ALUMINUM SILICATE; SORBITAN SESQUIOLEATE; PHENOXYETHANOL; ETHYLHEXYLGLYCERIN; MICA; TITANIUM DIOXIDE; AZADIRACHTA INDICA BARK; TURMERIC; HEMIDESMUS INDICUS ROOT; SPHAERANTHUS INDICUS FLOWERING TOP; PHYLLANTHUS EMBLICA FRUIT; ISOMETHYL-.ALPHA.-IONONE; BENZYL SALICYLATE; .BETA.-CITRONELLOL, (R)-; GERANIOL; .ALPHA.-HEXYLCINNAMALDEHYDE; LIMONENE, (+)-; LINALOOL, (+/-)-

Jafra Daily Skin Brightening antiperspirant roll-on

Active ingredient

Aluminum Chlorohydrate 12.3%

Purpose

Antiperspirant

Uses

Reduces underarm wetness

Warnings

For external use only
Do not use on broken skin
Stop use ifrash or irritation occurs
Ask a doctor before use if you havekidney disease

Keep out of reach of children.If swallowed, get medical help or contact a Poison Control Center right away.

Directions

Apply to underarms only

Inactive Ingredients

Water, PEG-40 Stearate, Stearic Acid, PEG-25 Propylene Glycol Stearate, Cetyl Alcohol, Magnesium Aluminum Silicate, Sorbitan Sesquioleate, Phenoxyethanol, Fragrance, Ethyhexylglycerin, Hexyl Cinnamal, Benzyl Salicylate, Limonene, Mica, Linalool, Citronellol, Titanium Dioxide, Alpha-Isomethyl Ionone, Geraniol, Azadirachta Indica Extract, Curcuma Longa Extract, Hemidesmus Indicus Extract, Sphaeranthus Indicus Extract, Phyllanthus Emblica Extract

Questions?Call 1-800-551-2345 or visit www.jafra.com